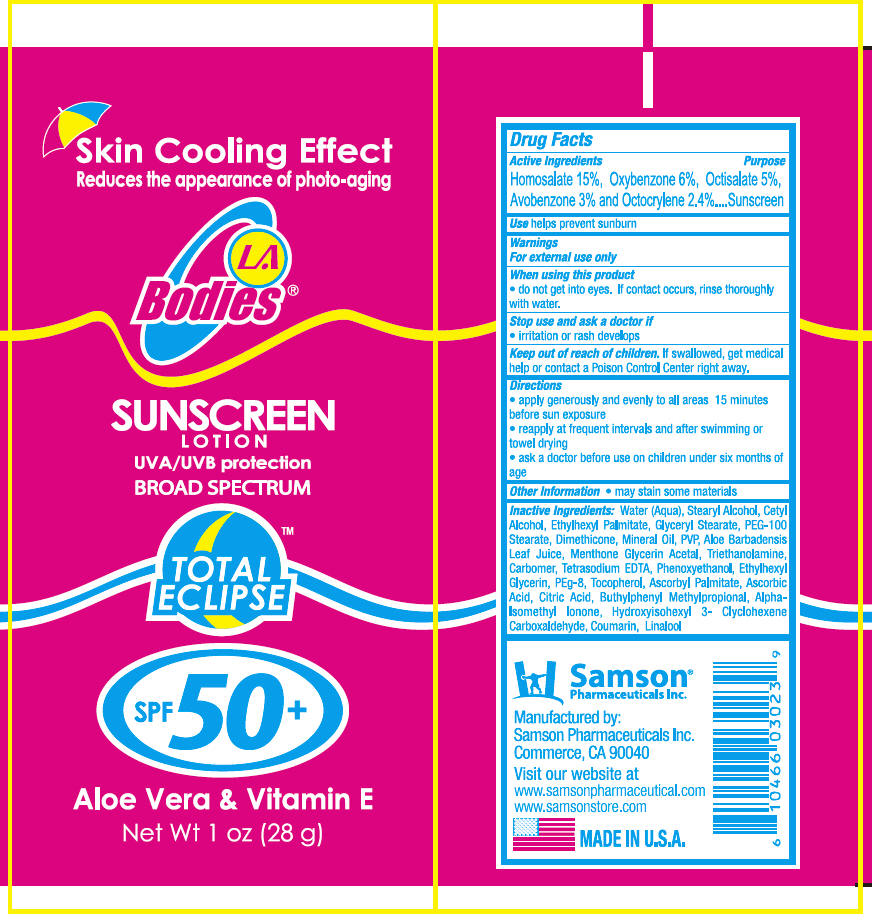 DRUG LABEL: LA Bodies Eclipse Sunscreen SPF 50
NDC: 20146-4008 | Form: LOTION
Manufacturer: SAMSON PHARMACEUTICAL
Category: otc | Type: HUMAN OTC DRUG LABEL
Date: 20240118

ACTIVE INGREDIENTS: Avobenzone 30 mg/1 g; Homosalate 150 mg/1 g; Octisalate 50 mg/1 g; Octocrylene 24 mg/1 g; Oxybenzone 60 mg/1 g
INACTIVE INGREDIENTS: water; stearyl alcohol; cetyl alcohol; glyceryl monostearate; PEG-100 stearate

LA Bodies® Eclipse Sunscreen Lotion SPF 50

Drug Facts

Active Ingredients

Homosalate 15%, Oxybenzone 6%, Octisalate 5%, Avobenzone 3% and Octocrylene 2.4%

Purpose

Sunscreen

Use

helps prevent sunburn

Warnings

For external use only

When using this product

- do not get into eyes. If contact occurs, rinse thoroughly with water.

Stop use and ask a doctor if

- irritation or rash develops

Keep out of reach of children. If swallowed, get medical help or contact a Poison Control Center right away.

Directions

- apply generously and evenly to all areas 15 minutes before sun exposure
- reapply at frequent intervals and after swimming or towel drying
- ask a doctor before use on children under six months of age

Other information

- may stain some materials

Inactive Ingredients

Water (Aqua), Stearyl Alcohol, Cetyl Alcohol, Ethylhexyl Palmitate, Glyceryl Stearate, PEG-100 Stearate, Dimethicone, Mineral Oil, PVP, Aloe Barbadensis Leaf Juice, Menthone Glycerin Acetal, Triethanolamine, Carbomer, Tetrasodium EDTA, Phenoxyethanol, Ethylhexyl Glycerin, PEg-8, Tocopherol, Ascorbyl Palmitate, Ascorbic Acid, Citric Acid, Buthylphenyl Methylpropional, Alpha-Isomethyl Ionone, Hydroxyisohexyl 3-Clyclohexene Carboxaldehyde, Coumarin, Linalool

Questions or Comments?

Call 1-877-888-8460

Manufactured by:
Samson Pharmaceuticals Inc.
Commerce, CA 90040

PRINCIPAL DISPLAY PANEL - 28 g Tube Label

Skin Cooling Effect
Reduces the appearance of photo-aging

LA
Bodies®

SUNSCREEN
LOTION
UVA/UVB protection
BROAD SPECTRUM

TOTAL
ECLIPSE

SPF 50+

Aloe Vera & Vitamin E
Net Wt 1 oz (28 g)